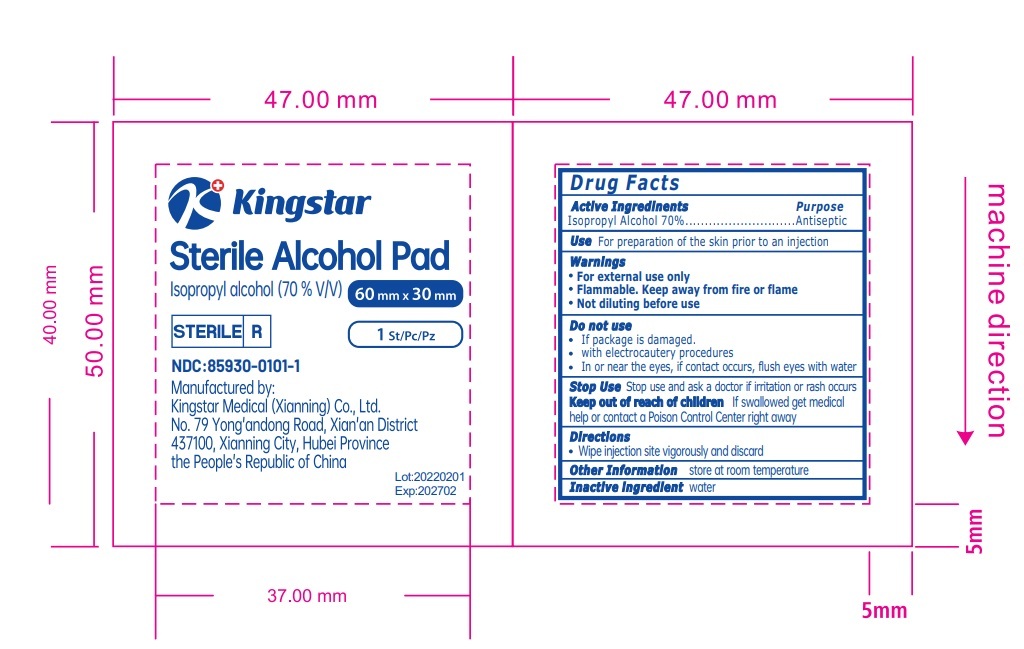 DRUG LABEL: Sterile alcohol pad
NDC: 85930-0101 | Form: PATCH
Manufacturer: Kingstar Medical (Xianning) Co., Ltd.
Category: otc | Type: HUMAN OTC DRUG LABEL
Date: 20250714

ACTIVE INGREDIENTS: ISOPROPYL ALCOHOL 0.7 mL/1 mL
INACTIVE INGREDIENTS: WATER

DOSAGE

lsopropyl alcohol (70 % v/v)

60 mm x 30 mm
1 St/Pc/Pz

Purpose

Antiseptic

Warnings

For external use only
Flammable. Keep away from fire or flame

Not diluting before use

Inactive ingredient

water

Use

For preparation of the skin prior to an injection

Keep out of reach of children

If swallowed get medical help or contact a Poison Control Center right away

PACKAGE LABEL

Kingstar Sterile Alcohol Pad

Isopropyl alcohol (70 % V/V) 60 mm x 30 mm

STERILE

1 St/PC/Pz

NDC:85930-0101-1

Manufactured by:Kingstar Mledical (Xianning) Co., Ltd.No.79 Yong'andong Road, Xian'an District 437100, Xianning City, Hubei Provincethe People's Republic of China

Lot:20220201

Exp:202702

Active Ingredient(s)

Isopropyl Alcohol 70%

Purpose

Antiseptic

Use

For preparation of the skin prior to an injection

Warnings

For external use only
Flammable. Keep away from fire or flame
Not diluting before use

Do not use

If package is damaged.
Not diluting before use
with electrocautery procedures
In or near the eyes, if contact occurs, flush eyes with water

Stop use

Stop use and ask a doctor if irritation or rash occurs

Keep out of reach of children If swallowed get medical help or contact a Poison Control Center right away

Directions

Wipe injection site vigorously and discard

Other information store at room temperature

Inactive ingredient water